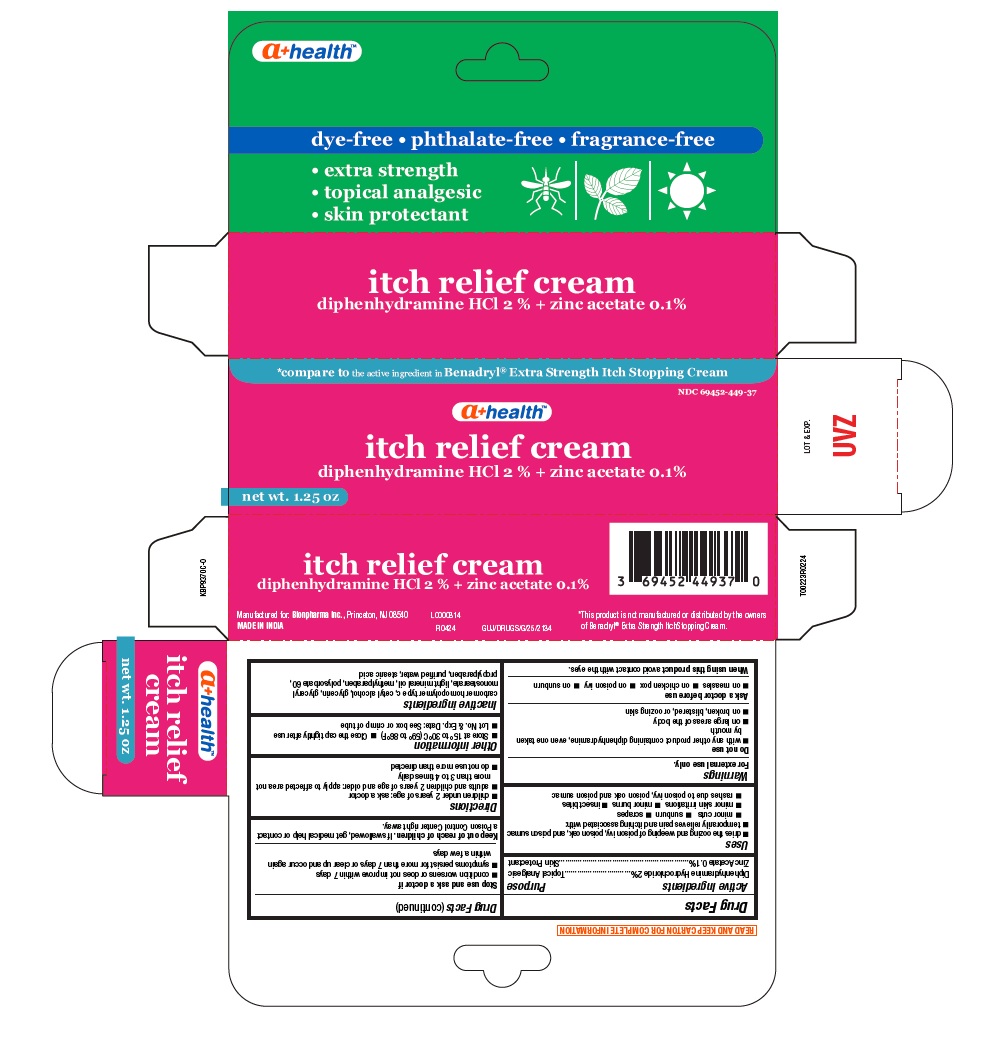 DRUG LABEL: itch relief
NDC: 69452-449 | Form: CREAM
Manufacturer: Bionpharma Inc.
Category: otc | Type: HUMAN OTC DRUG LABEL
Date: 20240716

ACTIVE INGREDIENTS: ZINC ACETATE 1 mg/1 g; DIPHENHYDRAMINE HYDROCHLORIDE 20 mg/1 g
INACTIVE INGREDIENTS: WATER; CARBOMER HOMOPOLYMER TYPE C; CETYL ALCOHOL; GLYCERIN; GLYCERYL MONOSTEARATE; LIGHT MINERAL OIL; METHYLPARABEN; POLYSORBATE 60; PROPYLPARABEN; STEARIC ACID

diphenhydramine HCl 2 % + zinc acetate 0.1%, A+ Health

Active ingredient

Diphenhydramine Hydrochloride 2%

Zinc Acetate 0.1%

Purpose

Topical Analgesic

Skin Protectant

Uses

■ dries the oozing and weeping of poison ivy, poison oak, and poison sumac

■ temporarily relieves pain and itching associated with:
■ minor cuts ■ sunburn ■ scrapes
■ minor skin irritations ■ minor burns ■ insect bites

■ rashes due to poison ivy, poison oak and poison sumac

Warnings

For external use only.

Do not use

■ with any other product containing diphenhydramine, even one taken by mouth
■ on large areas of the body
■ on broken, blistered, or oozing skin

Ask a doctor before use

■ on measles ■ on chicken pox ■ on poison ivy ■ on sunburn

When using this product

avoid contact with the eyes.

Stop use and ask a doctor if

■ condition worsens or does not improve within 7 days
■ symptoms persist for more than 7 days or clear up and occur again within a few days

Keep out of reach of children.

If swallowed, get medical help or contact a Poison Control Center right away.

Directions

■ children under 2 years of age: ask a doctor
■ adults and children 2 years of age and older: apply to affected area not more than 3 to 4 times daily

■ do not use more than directed

Other information

■ Store at 15° to 30°C (59° to 86°F) ■ Close the cap tightly after use
■ Lot No. & Exp. Date: See box or crimp of tube

Inactive ingredients

carbomer homopolymer type c, cetyl alcohol, glycerin, glyceryl monostearate, light mineral oil, methylparaben, polysorbate 60,
propylparaben, purified water, stearic acid

READ AND KEEP CARTON FOR COMPLETE INFORMATION

*This product is not manufactured or distributed by the owners of Benadryl® Extra Strength ItchStopping Cream.

Manufactured for: Bionpharma Inc., Princeton, NJ 08540

MADE IN INDIA

GUJ/DRUGS/G/25/2134

L0000814

R0424

LOT & EXP.

tube carton

* compare to the active ingredient in Benadryl® Extra Strength Itch Stopping Cream

NDC 69452-449-37

a+ healthTM

itch relief cream
diphenhydramine HCl 2 % + zinc acetate 0.1%

net wt. 1.25 oz

dye-free • phthalate-free • fragrance-free

• extra strength

• topical analgesic

• skin protectant